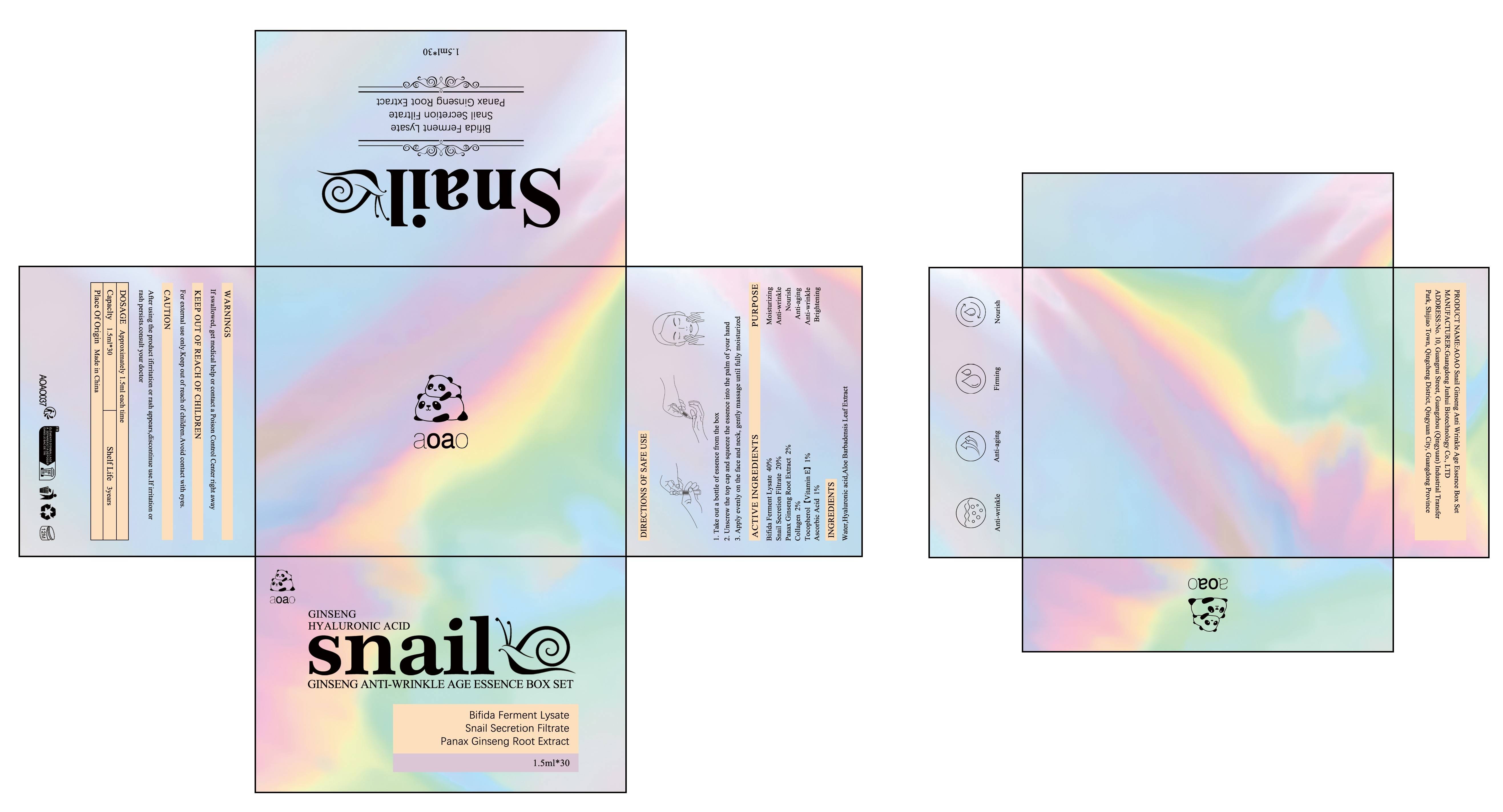 DRUG LABEL: AOAO Snail Ginseng Anti Wrinkle Age Essence Box Set
NDC: 84509-017 | Form: LIQUID
Manufacturer: Guangdong Junhui Biotechnology Co., LTD
Category: otc | Type: HUMAN OTC DRUG LABEL
Date: 20240921

ACTIVE INGREDIENTS: TOCOPHEROL 450 mg/45 mL; ASCORBIC ACID 450 mg/45 mL; FERMENT COMPLEX 6/PF 18000 mg/45 mL; COLLAGEN, SOLUBLE, FISH SKIN 900 mg/45 mL; ASIAN GINSENG 900 mg/45 mL; GARDEN SNAIL MUCIN 9000 mg/45 mL
INACTIVE INGREDIENTS: HYALURONIC ACID; ALOE VERA LEAF; WATER

Active Ingredients

Bifida Ferment Lysate 40%
Snail Secretion Filtrate 20%
Panax Ginseng Root Extract 2%
Collagen 2%
Tocopherol 1%
Ascorbic Acid 1%

Purpose

Moisturizing
Anti-wrinkle
Nourish
Anti-aging
Antif-ading
Brightening

Warnings

For external use only. Keep out ofreach of children.Avoid contact with eyes

Keep out of reach of children

If swallowed, get medical help or contact a Poison Control Center right away

CAUTION

After using the product ifirritation or rash appears,discontinue use.Ifirritation or
rash persists.consult your doctor.

DOSAGE

Approximately 1.5ml each time

Uses

1. Take out a bottle of essence from the box
2. Unscrew the top cap and squeeze the essence into the palm of your hand
3. Apply evenly on the face and neck, gently massage until fully moisturized

Product Name

AOAO Snail Ginseng Anti Wrinkle Age Essence Box Set

Inactive Ingredients

Water,Hyaluronic acid,Aloe Barbadensis Leaf Extract

MANUFACTURER

Guangdong Junhui Biotechnology Co., LTD

ADDRESS

No. 10, Guangrui Street, Guangzhou (Qingyuan) Industrial Transfer Park, Shijiao Town, Qingcheng District, Qingyuan City, Guangdong Province

Capacity

1.5ml*30

Shelf Life

3 years

Place of Origin

Made in China